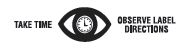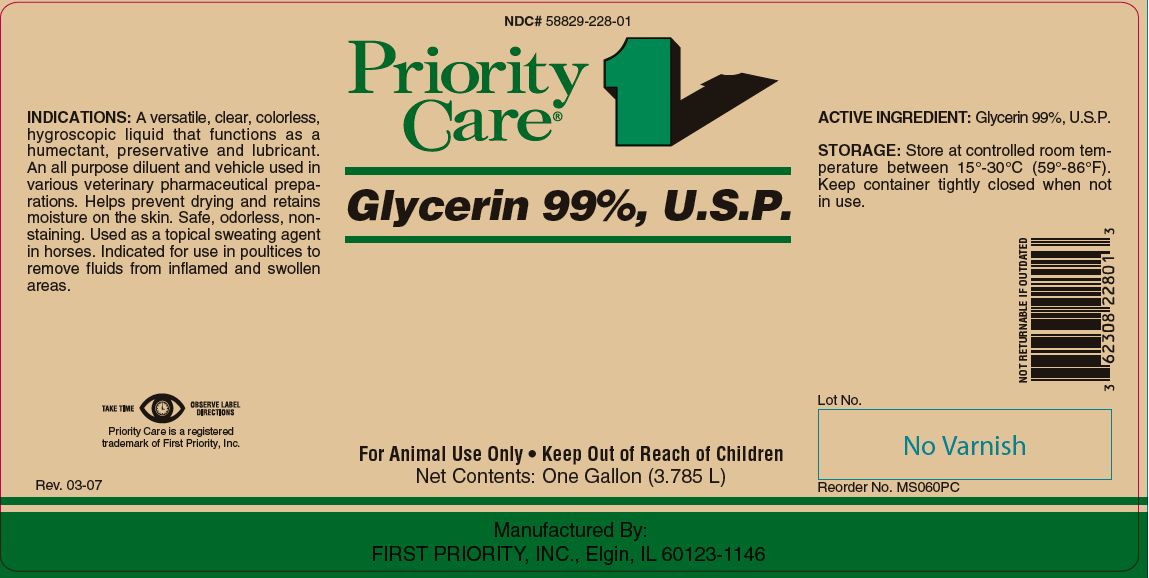 DRUG LABEL: Glycerin
NDC: 58829-228 | Form: LIQUID
Manufacturer: First Priority Incorporated
Category: animal | Type: OTC ANIMAL DRUG LABEL
Date: 20241028

ACTIVE INGREDIENTS: GLYCERIN 1241.6 g/1 L

Glycerin 99%, U.S.P.

KEEP OUT OF REACH OF CHILDREN

For Animal Use Only

Keep Out of Reach of Children

INDICATIONS:

A versatile, clear, colorless, hygroscopic liquid that functions as a humectant, preservative and lubricant. An all purpose diluent and vehicle used in various veterinary pharmaceutical preparations. Helps prevent drying and retains moisture on the skin. Safe, odorless, nonstaining. Used as a topical sweating agent in horses. Indicated for use in poultices to remove fluids from inflamed and swollen areas.

ACTIVE INGREDIENT:

Glycerin 99%, U.S.P.

STORAGE:

Store at controlled room temperature between 15°-30°C (59°-86°F). Keep container tightly closed when not in use.

Net Contents:

One Gallon (3.785 L) Reorder No. MS090PC

INFORMATION FOR OWNERS/CAREGIVERS

Priority Care is a registered trademark of First Priority, Inc.

Manufactured By: FIRST PRIORITY, INC., Elgin, IL 60123-1146